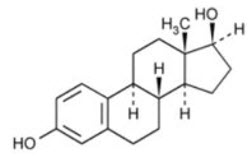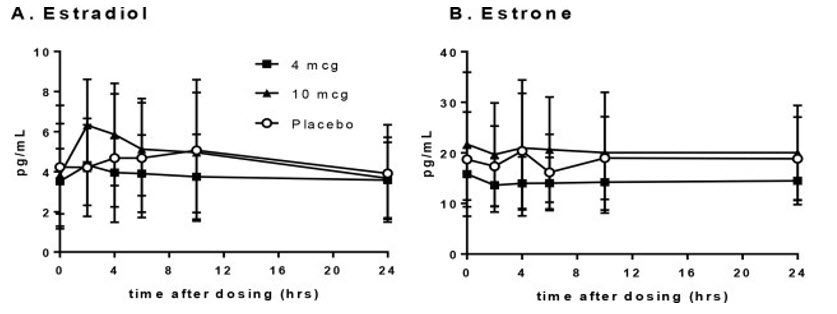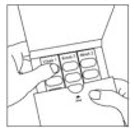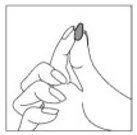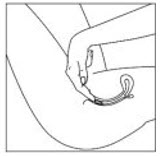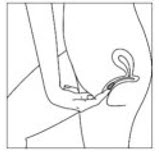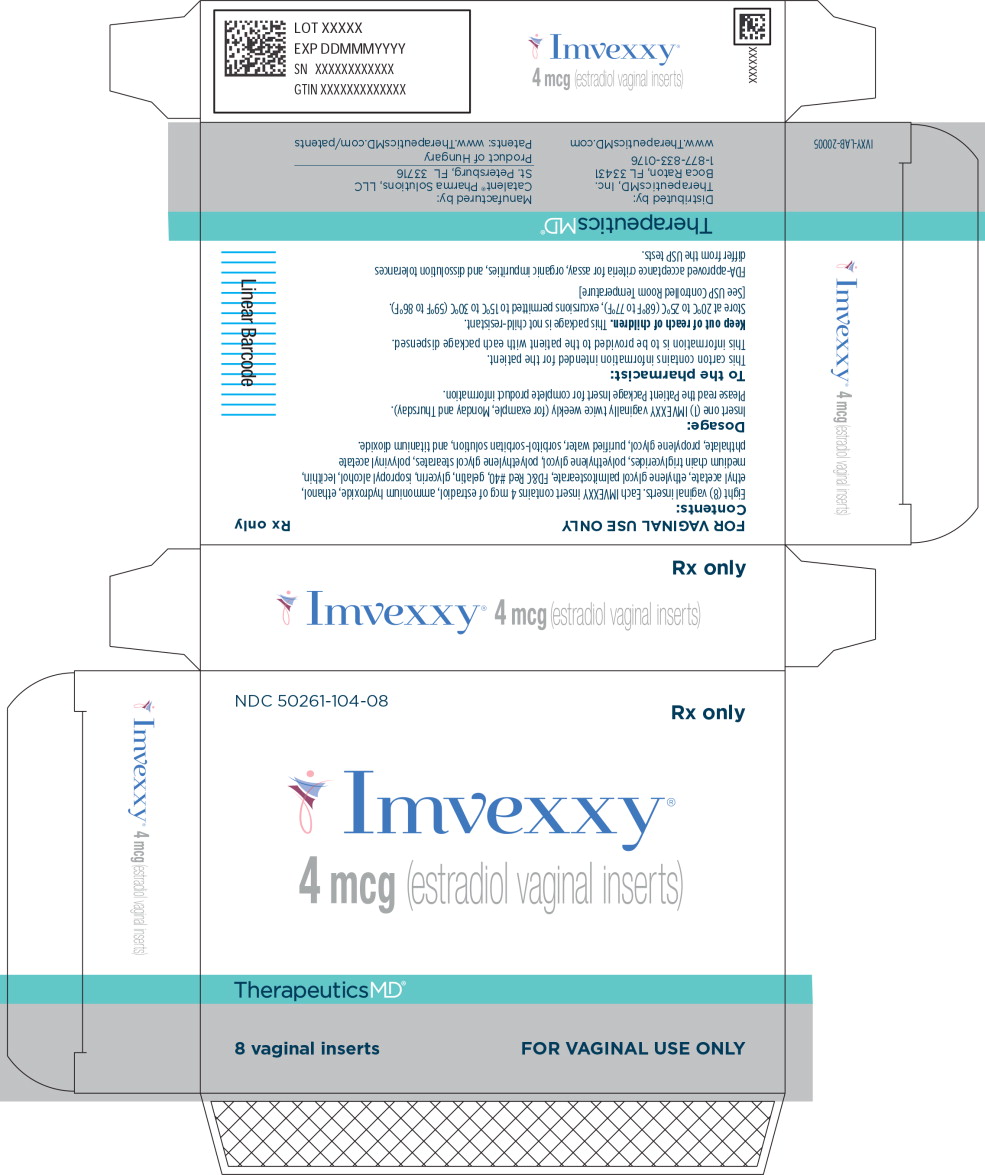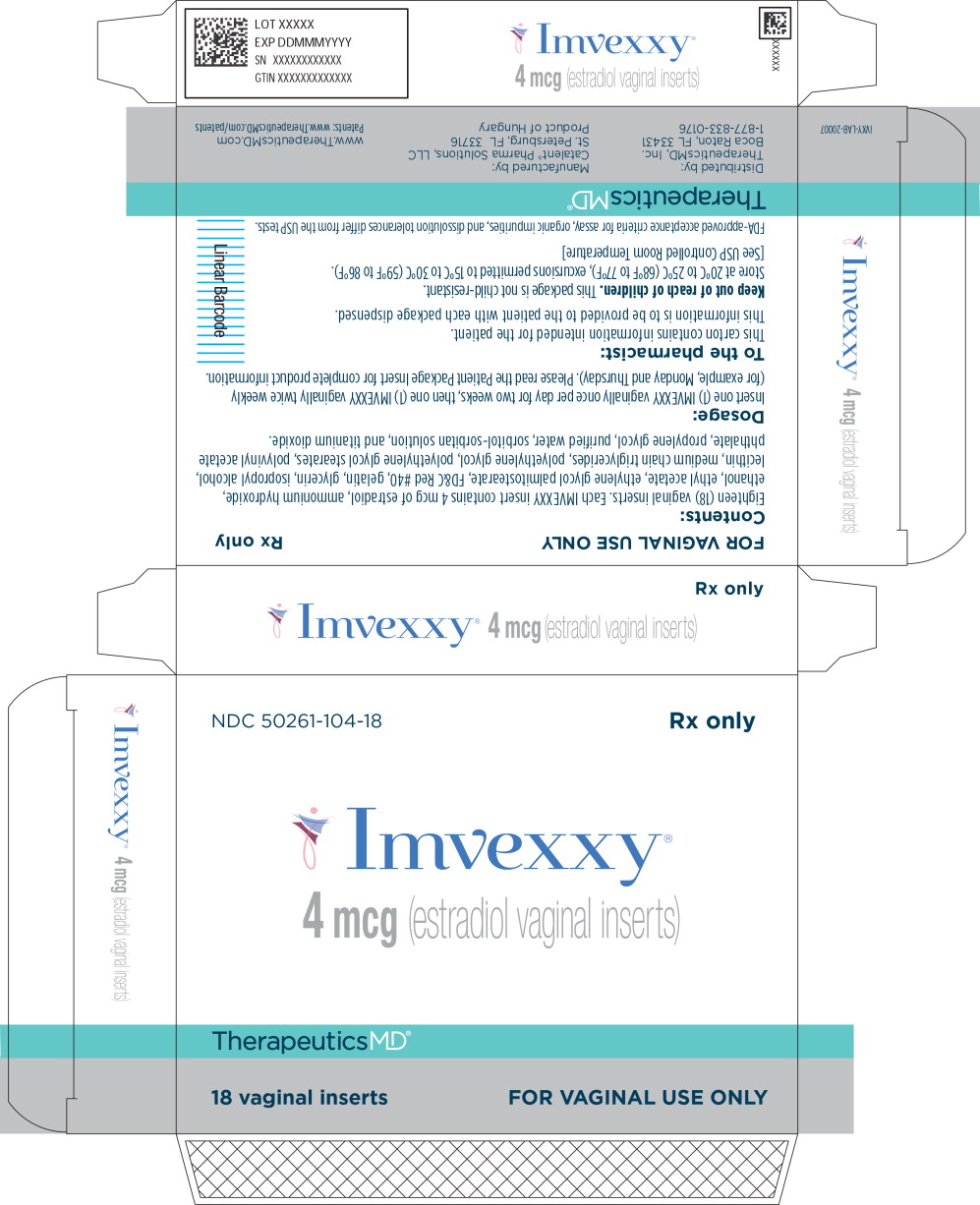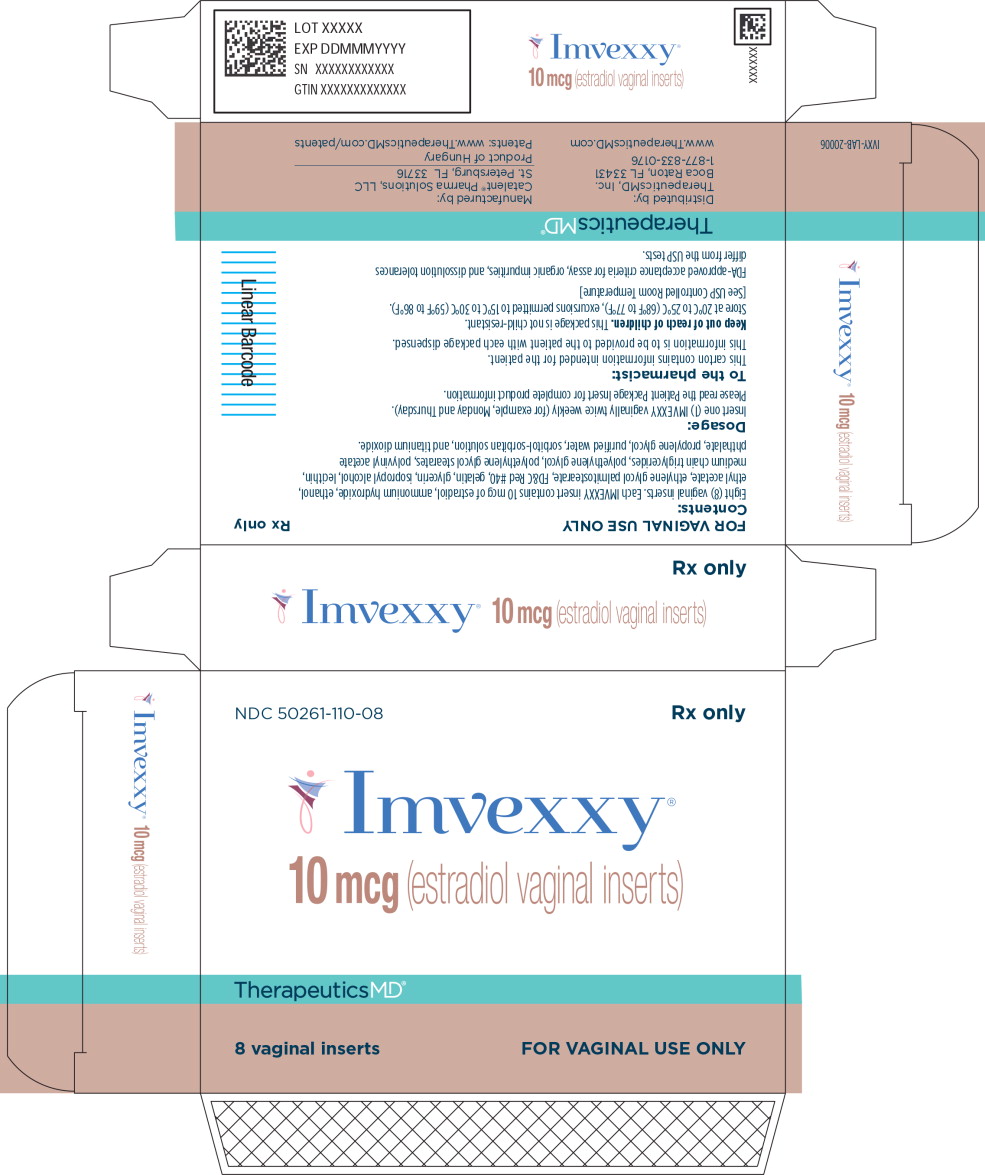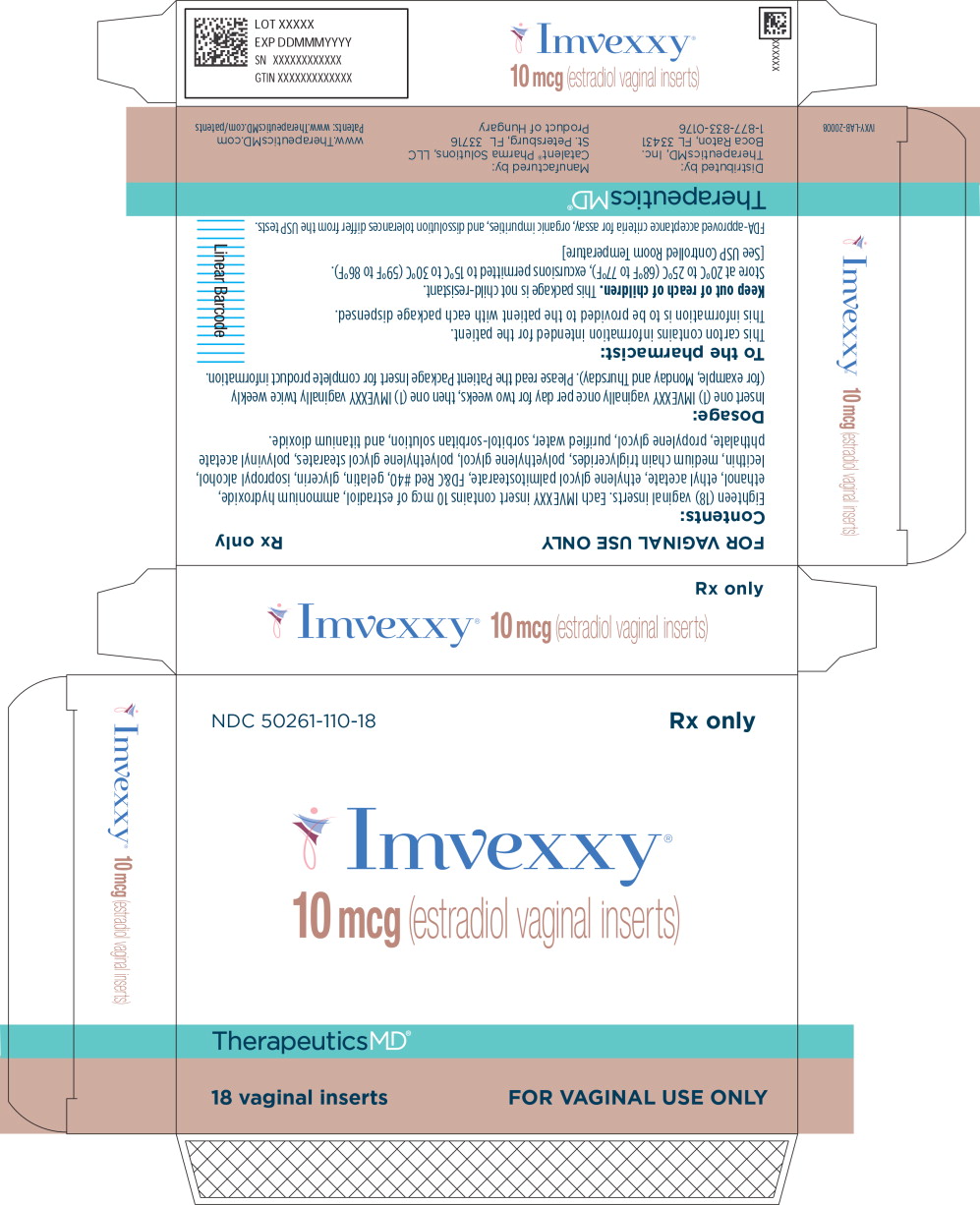 DRUG LABEL: IMVEXXY
NDC: 50261-104 | Form: INSERT
Manufacturer: Mayne Pharma LLC
Category: prescription | Type: HUMAN PRESCRIPTION DRUG LABEL
Date: 20250916

ACTIVE INGREDIENTS: ESTRADIOL 4 ug/1 1
INACTIVE INGREDIENTS: AMMONIA; ALCOHOL; LECITHIN, SOYBEAN; MEDIUM-CHAIN TRIGLYCERIDES; PEG-6 STEARATE; PEG-32 STEARATE; GLYCOL STEARATE; GELATIN, UNSPECIFIED; SORBITOL; SORBITAN; MANNITOL; GLYCERIN; FD&C RED NO. 40; TITANIUM DIOXIDE; WATER; ETHYL ACETATE; PROPYLENE GLYCOL; POLYVINYL ACETATE PHTHALATE; ISOPROPYL ALCOHOL; POLYETHYLENE GLYCOL, UNSPECIFIED

HIGHLIGHTS OF PRESCRIBING INFORMATION

These highlights do not include all the information needed to use IMVEXXY safely and effectively. See full prescribing information for IMVEXXY.
IMVEXXY®(estradiol vaginal inserts)
Initial U.S. Approval: 1975

WARNING: ENDOMETRIAL CANCER, CARDIOVASCULAR DISORDERS, PROBABLE DEMENTIA, and BREAST CANCER

See full prescribing information for complete boxed warning.

Estrogen-Alone Therapy

- There is an increased risk of endometrial cancer in a woman with a uterus who uses unopposed estrogens (5.3)
- The Women's Health Initiative (WHI) estrogen-alone substudy reported increased risks of stroke and deep vein thrombosis (DVT) (5.2)
- The WHI Memory Study (WHIMS) estrogen-alone ancillary study of WHI reported an increased risk of probable dementia in postmenopausal women 65 years of age and older (5.4)
- Do not use estrogen-alone therapy for the prevention of cardiovascular disease or dementia (5.2, 5.4)

Estrogen Plus Progestin Therapy

- The WHI estrogen plus progestin substudy reported increased risks of stroke, DVT, pumlonary embolism (PE) and myocardial infarction (MI) (5.2)
- The WHI estrogen plus progestin substudy reported increased risks of invasive breast cancer (5.3)
- The WHIMS estrogen plus progestin ancillary study of WHI reported an increased risk of probable dementia in postmenopausal women 65 years of age and older (5.4)
- Do not use estrogen plus progestogen therapy for the prevention of cardiovascular disease or dementia (5.2, 5.4)

RECENT MAJOR CHANGES

Boxed Warning | 11/2021
Warnings and Precautions, Malignant Neoplasms (5.3) | 11/2023

1 INDICATIONS AND USAGE

IMVEXXY is an estrogen indicated for the treatment of moderate to severe dyspareunia, a symptom of vulvar and vaginal atrophy, due to menopause (1).

2 DOSAGE AND ADMINISTRATION

Administer IMVEXXY intravaginally: 1 vaginal insert daily for 2 weeks, followed by 1 insert twice weekly (for example, Monday and Thursday). (2.1)

3 DOSAGE FORMS AND STRENGTHS

Vaginal inserts: 4 mcg or 10 mcg estradiol. (3)

4 CONTRAINDICATIONS

- Undiagnosed abnormal genital bleeding (4, 5.3)
- Breast cancer or a history of breast cancer (4, 5.3)
- Estrogen-dependent neoplasia (4, 5.3)
- Active DVT, PE, or history of these conditions (4, 5.2)
- Active arterial thromboembolic disease (for example, stroke or MI), or a history of these conditions (4, 5.2)
- Known anaphylactic reaction, angioedema, or hypersensitivity to IMVEXXY (4)
- Hepatic impairment or disease (4, 5.11)
- Protein C, protein S, or antithrombin deficiency, or other known thrombophilic disorders (4)

5 WARNINGS AND PRECAUTIONS

- Estrogens increase the risk of gallbladder disease (5.5)
- Discontinue estrogen if severe hypercalcemia, loss of vision, severe hypertriglyceridemia, or cholestatic jaundice occurs (5.6, 5.7, 5.10, 5.11)
- Monitor thyroid function in women on thyroid replacement hormone therapy (5.12, 5.19)

6 ADVERSE REACTIONS

The most common adverse reaction with IMVEXXY (incidence ≥ 3% and greater than placebo) is headache. (6.1)

To report SUSPECTED ADVERSE REACTIONS, contact TherapeuticsMD, Inc. at 1-888-228- 0150 or FDA at 1-800-FDA-1088 or www.fda.gov/medwatch.

7 DRUG INTERACTIONS

Inducers and inhibitors of CYP3A4 may affect estrogen drug metabolism and decrease or increase the estrogen plasma concentration. (7)

FULL PRESCRIBING INFORMATION

WARNING: ENDOMETRIAL CANCER, CARDIOVASCULAR DISORDERS, PROBABLE DEMENTIA, and BREAST CANCER

Estrogen-Alone Therapy

Endometrial Cancer

There is an increased risk of endometrial cancer in a woman with a uterus who uses unopposed estrogens. Adding a progestogen to estrogen therapy has been shown to reduce the risk of endometrial hyperplasia, which may be a precursor to endometrial cancer. Perform adequate diagnostic measures, including directed or random endometrial sampling when indicated, to rule out malignancy in postmenopausal women with undiagnosed persistent or recurring abnormal genital bleeding [see Warnings and Precautions (5.3)].

Cardiovascular Disorders and Probable Dementia

The Women's Health Initiative (WHI) estrogen-alone substudy reported increased risks of stroke and deep vein thrombosis (DVT) in postmenopausal women (50 to 79 years of age) during 7.1 years of treatment with daily oral conjugated estrogens (CE) [0.625 mg]-alone, relative to placebo [see Warnings and Precautions (5.2), and Clinical Studies (14.2)].

The WHI Memory Study (WHIMS) estrogen-alone ancil ary study of WHI reported an increased risk of developing probable dementia in postmenopausal women 65 years of age and older during 5.2 years of treatment with daily CE (0.625 mg)-alone, relative to placebo. It is unknown whether this finding applies to younger postmenopausal women [see Warnings and Precautions (5.4), Use in Specific Populations (8.5), and Clinical Studies (14.3)].

Do not use estrogen-alone therapy for the prevention of cardiovascular disease or dementia [see Warnings and Precautions (5.2, 5.4), and Clinical Studies (14.2, 14.3)] .

Only daily oral 0.625 mg CE was studied in the estrogen-alone substudy of the WHI. Therefore, the relevance of the WHI findings regarding adverse cardiovascular events and dementia to lower CE doses, other routes of administration, or other estrogen-alone products is not known. Without such data, it is not possible to definitively exclude these risks or determine the extent of these risks for other products. Discuss with your patient the benefits and risks of estrogen-alone therapy, taking into account her individual risk profile.

Prescribe estrogens with or without progestogens at the lowest effective doses and for the shortest duration consistent with treatment goals and risks for the individual woman.

Estrogen Plus Progestin Therapy

Cardiovascular Disorders and Probable Dementia

The WHI estrogen plus progestin substudy reported increased risks of DVT, pulmonary embolism (PE), stroke and myocardial infarction (MI) in postmenopausal women (50 to 79 years of age) during 5.6 years of treatment with daily oral CE (0.625 mg) combined with medroxyprogesterone acetate (MPA) [2.5 mg], relative to placebo [see Warnings and Precautions (5.2), and Clinical Studies (14.2)].

The WHIMS estrogen plus progestin ancillary study of the WHI, reported an increased risk of developing probable dementia in postmenopausal women 65 years of age and older during 4 years of treatment with daily CE (0.625 mg) combined with MPA (2.5 mg), relative to placebo. It is unknown whether this finding applies to younger postmenopausal women [see Warnings and Precautions (5.4), Use in Specific Populations (8.5), and Clinical Studies (14.3)].

Do not use estrogen plus progestogen therapy for the prevention of cardiovascular disease or dementia [see Warnings and Precautions (5.2, 5.4), and Clinical Studies (14.2, 14.3)] .

Breast Cancer

The WHI estrogen plus progestin substudy demonstrated an increased risk of invasive breast cancer [see Warnings and Precautions (5.3), and Clinical Studies (14.2)].

Only daily oral 0.625 mg CE and 2.5 mg MPA were studied in the estrogen plus progestin substudy of the WHI. Therefore, the relevance of the WHI findings regarding adverse cardiovascular events, dementia and breast cancer to lower CE plus other MPA doses, other routes of administration, or other estrogen plus progestogen products is not known. Without such data, it is not possible to definitively exclude these risks or determine the extent of these risks for other products. Discuss with your patient the benefits and risks of estrogen plus progestogen therapy, taking into account her individual risk profile.

Prescribe estrogens with or without progestogens at the lowest effective doses and for the shortest duration consistent with treatment goals and risks for the individual woman.

2 DOSAGE AND ADMINISTRATION

Generally, when estrogen is prescribed for a postmenopausal woman with a uterus, consider addition of a progestogen to reduce the risk of endometrial cancer.

Generally, a woman without a uterus does not need to use a progestogen in addition to her estrogen therapy. In some cases, however, hysterectomized women with a history of endometriosis may need a progestogen [see Warnings and Precautions (5.3, 5.15)] .

Use estrogen-alone, or in combination with a progestogen, at the lowest effective dose and for the shortest duration consistent with treatment goals and risks for the individual woman. Re-evaluate postmenopausal women periodically as clinically appropriate to determine if treatment is still necessary.

2.1 Treatment of Moderate to Severe Dyspareunia, a Symptom of Vulvar and Vaginal Atrophy, Due to Menopause

Generally, start therapy with the IMVEXXY 4 mcg dosage strength administered intravaginally; insert with the smaller end up for a depth of about two inches into the vaginal canal. Administer 1 insert daily at approximately the same time for 2 weeks, followed by 1 insert twice weekly, every three to four days (for example, Monday and Thursday). Make dosage adjustment based on the clinical response.

3 DOSAGE FORMS AND STRENGTHS

IMVEXXY are small, light pink, tear-shaped, vaginal inserts for manual placement into the vagina. IMVEXXY inserts contain 4 mcg or 10 mcg of estradiol. Each insert is imprinted in white ink on one side with "04" or "10" corresponding to the insert's dosage strength.

4 CONTRAINDICATIONS

IMVEXXY is contraindicated in women with any of the following conditions:

- Undiagnosed abnormal genital bleeding [see Warning and Precautions (5.3)].
- Breast cancer or a history of breast cancer [see Warnings and Precautions (5.3)].
- Estrogen-dependent neoplasia [see Warnings and Precautions (5.3)].
- Active DVT, PE, or history of these conditions [see Warnings and Precautions (5.2)].
- Active arterial thromboembolic disease (for example, stroke or MI), or a history of these conditions [see Warnings and Precautions (5.2)].
- Known anaphylactic reaction, angioedema, or hypersensitivity to IMVEXXY.
- Hepatic impairment or disease.
- Protein C, protein S, or antithrombin deficiency, or other known thrombophilic disorders.

5 WARNINGS AND PRECAUTIONS

5.1 Risks from Systemic Absorption

IMVEXXY is intended only for vaginal administration. Systemic absorption may occur with the use of IMVEXXY [see Pharmacokinetics (12.3)]. The warnings, precautions, and adverse reactions associated with the use of systemic estrogen-alone therapy should be taken into account.

5.2 Cardiovascular Disorders

Increased risks of stroke and DVT are reported with estrogen-alone therapy. Increased risks of PE, DVT, stroke, and MI are reported with estrogen plus progestin therapy. Immediately discontinue estrogen with or without progestogen therapy if any of these occur or are suspected.

Manage appropriately any risk factors for arterial vascular disease (for example, hypertension, diabetes mellitus, tobacco use, hypercholesterolemia, and obesity) and/or venous thromboembolism (VTE) (for example, personal history or family history of VTE, obesity, and systemic lupus erythematosus).

Stroke

The WHI estrogen-alone substudy reported a statistically significant increased risk of stroke in women 50 to 79 years of age receiving daily CE (0.625 mg)-alone compared to women in the same age group receiving placebo (45 versus 33 per 10,000 women-years, respectively). The increase in risk was demonstrated in year 1 and persisted [see Clinical Studies (14.2)] . Immediately discontinue estrogen-alone therapy if a stroke occurs or is suspected.

Subgroup analyses of women 50 to 59 years of age suggest no increased risk of stroke for those women receiving CE (0.625 mg)-alone versus those receiving placebo (18 versus 21 per 10,000 women-years).1

The WHI estrogen plus progestin substudy reported a statistically significant increased risk of stroke in women 50 to 79 years of age receiving daily CE (0.625 mg) plus MPA (2.5 mg) compared to women in the same age group receiving placebo (33 versus 25 per 10,000 women-years, respectively) [see Clinical Studies (14.2)] . The increase in risk was demonstrated after the first year and persisted.^1Immediately discontinue estrogen with or without progestogen therapy if a stroke occurs or is suspected.

Coronary Heart Disease

The WHI estrogen-alone substudy reported no overall effect on coronary heart disease (CHD) events (defined as nonfatal MI, silent MI, or CHD death) in women receiving estrogen-alone compared to placebo^2 [see Clinical Studies (14.2)] .

Subgroup analysis of women 50 to 59 years of age, who were less than 10 years since menopause, suggests a reduction (not statistically significant) of CHD events in those women receiving daily CE (0.625 mg)-alone compared to placebo (8 versus 16 per 10,000 women-years).^1

The WHI estrogen plus progestin substudy reported an increased risk (not statistically significant) of CHD events in women receiving daily CE (0.625 mg) plus MPA (2.5 mg) compared to women receiving placebo (41 versus 34 per 10,000 women-years).^1An increase in relative risk was demonstrated in year 1, and a trend toward decreasing relative risk was reported in years 2 through 5 [see Clinical Studies (14.2)] .

In postmenopausal women with documented heart disease (N = 2,763), average 66.7 years of age, in a controlled clinical trial of secondary prevention of cardiovascular disease (Heart and Estrogen/Progestin Replacement Study, HERS), treatment with daily CE (0.625 mg) plus MPA (2.5 mg) demonstrated no cardiovascular benefit. During an average follow-up of 4.1 years, treatment with CE plus MPA did not reduce the overall rate of CHD events in postmenopausal women with established CHD. There were more CHD events in the CE plus MPA-treated group than in the placebo group in year 1, but not during the subsequent years. Two thousand, three hundred and twenty-one (2,321) women from the original HERS trial agreed to participate in an open label extension of the original HERS, HERS II. Average follow-up in HERS II was an additional 2.7 years, for a total of 6.8 years overall. Rates of CHD events were comparable among women in the CE plus MPA group and the placebo group in HERS, HERS II, and overall.

Venous Thromboembolism

In the WHI estrogen-alone substudy, the risk of VTE (DVT and PE) was increased for women receiving daily CE (0.625 mg)-alone compared to placebo (30 versus 22 per 10,000 women-years), although only the increased risk of DVT reached statistical significance (23 versus 15 per 10,000 women-years). The increase in VTE risk was demonstrated during the first 2 years^3 [see Clinical Studies (14.2)] . Immediately discontinue estrogen-alone therapy if a VTE occurs or is suspected.

The WHI estrogen plus progestin substudy reported a statistically significant 2-fold greater rate of VTE in women receiving daily CE (0.625 mg) plus MPA (2.5 mg) compared to women receiving placebo (35 versus 17 per 10,000 women-years). Statistically significant increases in risk for both DVT (26 versus 13 per 10,000 women-years) and PE (18 versus 8 per 10,000 women-years) were also demonstrated. The increase in VTE risk was demonstrated during the first year and persisted^4 [see Clinical Studies (14.2)] . Immediately discontinue estrogen plus progestogen therapy if a VTE occurs or is suspected.

If feasible, discontinue estrogens at least 4 to 6 weeks before surgery of the type associated with an increased risk of thromboembolism, or during periods of prolonged immobilization.

5.3 Malignant Neoplasms

Endometrial Cancer

An increased risk of endometrial cancer has been reported with the use of unopposed estrogen therapy in a woman with a uterus. The reported endometrial cancer risk among unopposed estrogen users is about 2- to 12-fold greater than in non-users and appears dependent on duration of treatment and on estrogen dose. Most studies show no significant increased risk associated with use of estrogens for less than 1 year. The greatest risk appears associated with prolonged use, with an increased risk of 15- to 24- fold for 5 to 10 years or more, and this risk has been shown to persist for at least 8 to 15 years after estrogen therapy is discontinued.

Clinical surveillance of all women using estrogen-alone or estrogen plus progestogen therapy is important. Perform adequate diagnostic measures, including directed or random endometrial sampling when indicated, to rule out malignancy in postmenopausal women with undiagnosed persistent or recurring abnormal genital bleeding.

There is no evidence that the use of natural estrogens results in a different endometrial risk profile than synthetic estrogens of equivalent estrogen dose. Adding a progestogen to estrogen therapy in postmenopausal women has been shown to reduce the risk of endometrial hyperplasia, which may be a precursor to endometrial cancer.

Breast Cancer

The WHI substudy of daily CE (0.625 mg)-alone provided information about breast cancer in estrogen-alone users. In the WHI estrogen-alone substudy, after an average follow-up of 7.1 years, daily CE-alone was not associated with an increased risk of invasive breast cancer [relative risk (RR) 0.80]^5 [see Clinical Studies (14.2)] .

After a mean follow-up of 5.6 years, the WHI substudy of daily CE (0.625 mg) plus MPA (2.5 mg) reported an increased risk of invasive breast cancer in women who took daily CE plus MPA compared to placebo. In this substudy, prior use of estrogen-alone or estrogen plus progestin therapy was reported by 26% of the women. The relative risk of invasive breast cancer was 1.24, and the absolute risk was 41 versus 33 cases per 10,000 women-years, for CE plus MPA compared with placebo. Among women who reported prior use of hormone therapy, the relative risk of invasive breast cancer was 1.86, and the absolute risk was 46 versus 25 cases per 10,000 women-years, for CE plus MPA compared with placebo. Among women who reported no prior use of hormone therapy, the relative risk of invasive breast cancer was 1.09, and the absolute risk was 40 versus 36 cases per 10,000 women-years for CE plus MPA compared with placebo. In the same substudy, invasive breast cancers were larger, were more likely to be node positive, and were diagnosed at a more advanced stage in the CE (0.625 mg) plus MPA (2.5 mg) group compared with the placebo group. Metastatic disease was rare, with no apparent difference between the two groups. Other prognostic factors, such as histologic subtype, grade and hormone receptor status did not differ between the groups^6 [see Clinical Studies (14.2)] .

Consistent with the WHI clinical trial, observational studies have also reported an increased risk of breast cancer for estrogen plus progestin therapy, and a smaller increased risk for estrogen-alone therapy, after several years of use. One large meta-analysis of prospective cohort studies reported increased risks that were dependent upon duration of use and could last up to >10 years after discontinuation of estrogen plus progestin therapy and estrogen-alone therapy. Extension of the WHI trials also demonstrated increased breast cancer risk associated with estrogen plus progestin therapy. Observational studies also suggest that the risk of breast cancer was greater, and became apparent earlier, with estrogen plus progestin therapy as compared to estrogen-alone therapy. These studies have not generally found significant variation in the risk of breast cancer among different estrogen plus progestin combinations, doses, or routes of administration.

The use of estrogen-alone and estrogen plus progestin therapy has been reported to result in an increase in abnormal mammograms requiring further evaluation.

All women should receive yearly breast examinations by a healthcare provider and perform monthly breast self-examinations. In addition, mammography examinations should be scheduled based on patient age, risk factors, and prior mammogram results.

Ovarian Cancer

The CE plus MPA substudy of WHI reported that estrogen plus progestin increased the risk of ovarian cancer. After an average follow-up of 5.6 years, the relative risk for ovarian cancer for CE plus MPA versus placebo was 1.58 (95% confidence interval [CI], 0.77 to 3.24), but it was not statistically significant. The absolute risk for CE plus MPA versus placebo was 4 versus 3 cases per 10,000 women-years.^7

A meta-analysis of 17 prospective and 35 retrospective epidemiology studies found that women who used hormonal therapy for menopausal symptoms had an increased risk for ovarian cancer. The primary analysis, using case-control comparisons, included 12,110 cancer cases from the 17 prospective studies. The relative risks associated with current use of hormonal therapy was 1.41 (95% CI 1.32 to 1.50); there was no difference in the risk estimates by duration of the exposure (less than 5 years [median of 3 years] vs. greater than 5 years [median of 10 years] of use before the cancer diagnosis). The relative risk associated with combined current and recent use (discontinued use within 5 years before cancer diagnosis) was 1.37 (95% CI, 1.27 to 1.48), and the elevated risk was significant for both estrogen-alone and estrogen plus progestin products. The exact duration of hormone therapy use associated with an increased risk of ovarian cancer, however, is unknown.

5.4 Probable Dementia

In the WHI Memory Study (WHIMS) estrogen-alone ancillary study, a population of 2,947 hysterectomized women 65 to 79 years of age was randomized to daily CE (0.625 mg)- alone or placebo.

After an average follow-up of 5.2 years, 28 women in the estrogen-alone group and 19 women in the placebo group were diagnosed with probable dementia. The relative risk of probable dementia for CE-alone versus placebo was 1.49 (95% CI, 0.83 to 2.66). The absolute risk of probable dementia for CE-alone versus placebo was 37 versus 25 cases per 10,000 women-years^8 [see Use in Specific Populations (8.5), and Clinical Studies (14.3)] .

In the WHIMS estrogen plus progestin ancillary study, a population of 4,532 postmenopausal women 65 to 79 years of age was randomized to daily CE (0.625 mg) plus MPA (2.5 mg) or placebo. After an average follow-up of 4 years, 40 women in the CE plus MPA group and 21 women in the placebo group were diagnosed with probable dementia. The relative risk of probable dementia for CE plus MPA versus placebo was 2.05 (95% CI, 1.21 to 3.48). The absolute risk of probable dementia for CE plus MPA versus placebo was 45 versus 22 cases per 10,000 women-years^8 [see Use in Specific Populations (8.5), and Clinical Studies (14.3)] .

When data from the two populations in the WHIMS estrogen-alone and estrogen plus progestin ancillary studies were pooled as planned in the WHIMS protocol, the reported overall relative risk for probable dementia was 1.76 (95% CI, 1.19 to 2.60). Since both ancillary studies were conducted in women 65 to 79 years of age, it is unknown whether these findings apply to younger postmenopausal women^8 [see Use in Specific Populations (8.5), and Clinical Studies (14.3)] .

5.5 Gallbladder Disease

A 2- to 4-fold increase in the risk of gallbladder disease requiring surgery in postmenopausal women receiving estrogens has been reported.

5.6 Hypercalcemia

Estrogen administration may lead to severe hypercalcemia in women with breast cancer and bone metastases. Discontinue estrogens, including IMVEXXY, if hypercalcemia occurs and take appropriate measures to reduce the serum calcium level.

5.7 Visual Abnormalities

Retinal vascular thrombosis has been reported in women receiving estrogens. Discontinue IMVEXXY pending examination if there is a sudden partial or complete loss of vision, or a sudden onset of proptosis, diplopia, or migraine. Permanently discontinue estrogens, including IMVEXXY, if examination reveals papilledema or retinal vascular lesions.

5.8 Addition of a Progestogen When a Woman Has Not Had a Hysterectomy

Studies of the addition of a progestogen for 10 or more days of a cycle of estrogen administration, or daily with estrogen in a continuous regimen, have reported a lowered incidence of endometrial hyperplasia than would be induced by estrogen treatment alone. Endometrial hyperplasia may be a precursor to endometrial cancer.

There are, however, possible risks that may be associated with the use of progestogens with estrogens compared to estrogen-alone regimens. These include an increased risk of breast cancer.

5.9 Elevated Blood Pressure

In a small number of case reports, substantial increases in blood pressure have been attributed to idiosyncratic reactions to estrogens. In a large, randomized, placebo-controlled clinical trial, a generalized effect of estrogens on blood pressure was not seen.

5.10 Exacerbation of Hypertriglyceridemia

In women with pre-existing hypertriglyceridemia, estrogen therapy may be associated with elevations of plasma triglycerides leading to pancreatitis. Discontinue IMVEXXY if pancreatitis occurs.

5.11 Hepatic Impairment and/or Past History of Cholestatic Jaundice

Estrogens may be poorly metabolized in women with hepatic impairment. Exercise caution in any woman with a history of cholestatic jaundice associated with past estrogen use or with pregnancy. In the case of recurrence of cholestatic jaundice, discontinue IMVEXXY.

5.12 Exacerbation of Hypothyroidism

Estrogen administration leads to increased thyroid-binding globulin (TBG) levels. Women with normal thyroid function can compensate for the increased TBG by making more thyroid hormone, thus maintaining free T4 and T3 serum concentrations in the normal range. Women dependent on thyroid hormone replacement therapy who are also receiving estrogens may require increased doses of their thyroid replacement therapy. Monitor thyroid function in these women during treatment with IMVEXXY to maintain their free thyroid hormone levels in an acceptable range.

5.13 Fluid Retention

Estrogens may cause some degree of fluid retention. Monitor any woman with a condition(s) that might predispose her to fluid retention, such as cardiac or renal impairment. Discontinue estrogen-alone therapy, including IMVEXXY, with evidence of medically concerning fluid retention.

5.14 Hypocalcemia

Estrogen-induced hypocalcemia may occur in women with hypoparathyroidism. Consider whether the benefits of estrogen therapy, including IMVEXXY, outweigh the risks in such women.

5.15 Exacerbation of Endometriosis

A few cases of malignant transformation of residual endometrial implants have been reported in women treated post-hysterectomy with estrogen-alone therapy. Consider the addition of progestogen therapy for women known to have residual endometriosis post-hysterectomy.

5.16 Hereditary Angioedema

Exogenous estrogens may exacerbate symptoms of angioedema in women with hereditary angioedema. Consider whether the benefits of estrogen therapy, including IMVEXXY, outweigh the risks in such women.

5.17 Exacerbation of Other Conditions

Estrogen therapy, including IMVEXXY, may cause an exacerbation of asthma, diabetes mellitus, epilepsy, migraine, porphyria, systemic lupus erythematosus, and hepatic hemangiomas. Consider whether the benefits of estrogen therapy outweigh the risks in women with these conditions.

5.18 Laboratory Test

Serum follicle stimulating hormone (FSH) and estradiol levels have not been shown to be useful in the management of postmenopausal women with moderate to severe symptoms of vulvar and vaginal atrophy due to menopause.

5.19 Drug Laboratory Test Interactions

- Accelerated prothrombin time, partial thromboplastin time, and platelet aggregation time; increased platelet count; increased factors II, VII antigen, VIII antigen, VIII coagulant activity, IX, X, XII, VII-X complex, II-VII-X complex, and beta- thromboglobulin; decreased levels of antifactor Xa and antithrombin III, decreased antithrombin III activity; increased levels of fibrinogen and fibrinogen activity; increased plasminogen antigen and activity.
- Increased thyroid-binding globulin (TBG) levels leading to increased circulating total thyroid hormone as measured by protein-bound iodine (PBI), T4 levels (by column or by radioimmunoassay) or T3 levels by radioimmunoassay. T3 resin uptake is decreased, reflecting the elevated TBG. Free T4 and free T3 concentrations are unaltered. Women on thyroid replacement therapy may require higher doses of thyroid hormone.
- Other binding proteins may be elevated in serum, for example, corticosteroid binding globulin (CBG), sex hormone-binding globulin (SHBG), leading to increased total circulating corticosteroids and sex steroids, respectively. Free hormone concentrations, such as testosterone and estradiol, may be decreased. Other plasma proteins may be increased (angiotensinogen/renin substrate, alpha-1-antitrypsin, ceruloplasmin).
- Increased plasma high-density lipoprotein (HDL) and HDL2 cholesterol subfraction concentrations, reduced low-density lipoprotein (LDL) cholesterol concentrations, increased triglyceride levels.
- Impaired glucose tolerance.

6 ADVERSE REACTIONS

The following serious adverse reactions are discussed elsewhere in the labeling:

- Cardiovascular Disorders [see Boxed Warning, Warnings and Precautions (5.2)].
- Malignant Neoplasms [see Boxed Warning, Warnings and Precautions (5.3)] .

6.1 Clinical Trials Experience

Because clinical trials are conducted under widely varying conditions, adverse reaction rates observed in the clinical trials of a drug cannot be directly compared to rates in the clinical trials of another drug and may not reflect the rates observed in practice.

The safety of IMVEXXY 4 mcg and 10 mcg was assessed in a single, double-blind, parallel-group, placebo-controlled trial (N = 382). The duration of treatment in this trial was 12 weeks (dosing occurred every day for 14 days and then twice weekly thereafter for maintenance).

Adverse reactions with an incidence of ≥ 3% in any IMVEXXY group and numerically greater than those reported in the placebo group are listed in Table 1.

Table 1: Treatment-Emergent Adverse Reactions Reported at a Frequency of ≥ 3% and Numerical y More Common in Women Receiving IMVEXXY
Preferred Term | IMVEXXY 4 mcg (N = 191) | IMVEXXY 10 mcg (N = 191) | Placebo (N = 192)
Nervous system disorders, n (%)
Headache | 7 (3.7) | 5 (2.6) | 6 (3.1)

6.2 Postmarketing Experience

The following adverse reactions have been identified during post-approval use of IMVEXXY 4 and 10 mcg. Because these reactions are reported voluntarily from a population of uncertain size, it is not always possible to reliably estimate their frequency or establish a causal relationship to drug exposure.

Genitourinary system

Vaginal discharge.

7 DRUG INTERACTIONS

In vitro and in vivo studies have shown that estrogens are metabolized partially by cytochrome P450 3A4 (CYP3A4). Therefore, inducers or inhibitors of CYP3A4 may affect estrogen drug metabolism. Inducers of CYP3A4, such as St. John's wort (Hypericum perforatum) preparations, phenobarbital, carbamazepine, and rifampin, may reduce plasma concentrations of estrogens, possibly resulting in a decrease in therapeutic effects and/or changes in the uterine bleeding profile. Inhibitors of CYP3A4 such as erythromycin, clarithromycin, ketoconazole, itraconazole, ritonavir and grapefruit juice may increase plasma concentrations of estrogens and may result in side effects.

8 USE IN SPECIFIC POPULATIONS

8.1 Pregnancy

Risk Summary

IMVEXXY is not indicated for use in pregnancy. There are no data with the use of IMVEXXY in pregnant women; however, epidemiologic studies and meta-analyses have not found an increased risk of genital or nongenital birth defects (including cardiac anomalies and limb-reduction defects) following exposure to combined hormonal contraceptives (estrogens and progestins) before conception or during early pregnancy.

In the U.S. general population, the estimated background risk of major birth defects and miscarriage in clinically recognized pregnancies is 2% to 4% and 15% to 20%, respectively.

8.2 Lactation

Risk Summary

Estrogens are present in human milk and can reduce milk production in breast-feeding females. This reduction can occur at any time but is less likely to occur once breast- feeding is well-established. The developmental and health benefits of breastfeeding should be considered along with the mother's clinical need for IMVEXXY and any potential adverse effects on the breastfed child from IMVEXXY or from the underlying maternal condition.

8.4 Pediatric Use

IMVEXXY is not indicated for use in pediatric patients. Clinical studies have not been conducted in the pediatric population.

8.5 Geriatric Use

There have not been sufficient numbers of geriatric women involved in clinical studies utilizing IMVEXXY to determine whether those over 65 years of age differ from younger subjects in their response to IMVEXXY.

The Women's Health Initiative Studies

In the WHI estrogen-alone substudy (daily CE [0.625 mg]-alone versus placebo), there was a higher relative risk of stroke in women greater than 65 years of age [see Clinical Studies (14.2)] .

In the WHI estrogen plus progestin substudy (daily CE [0.625 mg] plus MPA [2.5 mg] versus placebo), there was a higher relative risk of nonfatal stroke and invasive breast cancer in women greater than 65 years of age [see Clinical Studies (14.2)] .

The Women's Health Initiative Memory Study

In the WHIMS ancillary studies of postmenopausal women 65 to 79 years of age, there was an increased risk of developing probable dementia in women receiving estrogen- alone or estrogen plus progestin when compared to placebo [see Warnings and Precautions (5.4), and Clinical Studies (14.3)] .

Since both ancillary studies were conducted in women 65 to 79 years of age, it is unknown whether these findings apply to younger postmenopausal women^8 [see Warnings and Precautions (5.4), and Clinical Studies (14.3)] .

10 OVERDOSAGE

Overdosage of estrogen may cause nausea, vomiting, breast tenderness, abdominal pain, drowsiness and fatigue, and withdrawal bleeding may occur in women. Treatment of overdose consists of discontinuation of IMVEXXY therapy with institution of appropriate symptomatic care.

11 DESCRIPTION

IMVEXXY (estradiol vaginal inserts) are small, light pink, tear-shaped, vaginal inserts for manual placement into the vagina. Inserts contain 4 mcg or 10 mcg of estradiol, an estrogen. Each insert is imprinted in white ink on one side with "04" or "10" corresponding to the insert's dosage strength. IMVEXXY vaginal inserts are used intravaginally. When the insert comes in contact with the vaginal mucosa, estradiol is released into the vagina.

Estradiol is chemically described as estra-1,3,5 (10)-triene-3,17β-diol. The chemical formula is C18H24O2with a molecular weight of 272.38.

The structural formula is:

IMVEXXY (estradiol vaginal inserts) contain the following inactive ingredients: ammonium hydroxide, ethanol, ethyl acetate, ethylene glycol palmitostearate, FD&C Red #40, gelatin, glycerin, isopropyl alcohol, lecithin, medium chain triglycerides, polyethylene glycol, polyethylene glycol stearates, polyvinyl acetate phthalate, propylene glycol, purified water, sorbitol-sorbitan solution, and titanium dioxide. FDA approved acceptance criteria for assay, organic impurities, and dissolution tolerances differ from the USP test.

12 CLINICAL PHARMACOLOGY

12.1 Mechanism of Action

Endogenous estrogens are largely responsible for the development and maintenance of the female reproductive system and secondary sexual characteristics. Although circulating estrogens exist in a dynamic equilibrium of metabolic interconversions, estradiol is the principal intracellular human estrogen and is substantially more potent than its metabolites, estrone and estriol, at the receptor level.

The primary source of estrogen in normally cycling adult women is the ovarian follicle, which secretes 70 to 500 mcg of estradiol daily, depending on the phase of the menstrual cycle. After menopause, most endogenous estrogen is produced by conversion of androstenedione, secreted by the adrenal cortex, to estrone in the peripheral tissues. Thus, estrone and the sulfate conjugated form, estrone sulfate, are the most abundant circulating estrogens in postmenopausal women.

Estrogens act through binding to nuclear receptors in estrogen-responsive tissues. To date, two estrogen receptors have been identified. These vary in proportion from tissue to tissue.

Circulating estrogens modulate the pituitary secretion of the gonadotropins, luteinizing hormone (LH), and FSH, through a negative feedback mechanism. Estrogens act to reduce the elevated levels of these hormones seen in postmenopausal women.

12.2 Pharmacodynamics

Generally, a serum estrogen concentration does not predict an individual woman's therapeutic response to IMVEXXY nor her risk for adverse outcomes. Likewise, exposure comparisons across different estrogen products to infer efficacy or safety for the individual woman may not be valid.

12.3 Pharmacokinetics

Absorption

Estrogen drug products are well absorbed through the skin, mucous membranes, and the gastrointestinal tract. The vaginal delivery of estrogens circumvents first-pass metabolism.

In a multicenter, double-blind placebo-controlled study of 574 postmenopausal women randomized to placebo, or 4 and 10 mcg of IMVEXXY, a subset of 54 women participated in a pharmacokinetics substudy. Women received 1 vaginal insert daily for the first 2 weeks, followed by 1 insert twice weekly for the following 10 weeks.

Mean (±SD) serum estradiol and estrone following 14 days of once daily administration of IMVEXXY are shown in Figure 1. Administration of the 4 mcg and 10 mcg IMVEXXY vaginal inserts and placebo once daily for 14 days resulted in a mean estradiol Cavg (0-24)of 3.6, 4.6, and 4.3 pg/mL, respectively, Table 2.

Figure 1: Mean (±SD) Serum Concentration of Estradiol and Estrone on Day 14 Following Daily Administration of IMVEXXY 4 mcg, IMVEXXY 10 mcg, and Placebo

Table 2: Arithmetic Mean (SD) of Estradiol and Estrone Pharmacokinetic Parameters Following 14 Daily Doses – Unadjusted for Baseline
 | Estradiol |  | Estrone
 | Cmax (pg/mL) | Cavg (0-24) (pg/mL) | Cmax (pg/mL) | Cavg (0-24) (pg/mL)
4 mcg | 4.8 (2.3) | 3.6 (1.8) | 16.0 (5.5) | 13.6 (4.8)
10 mcg | 7.3 (2.4) | 4.6 (2.3) | 23.9 (13.5) | 19.3 (10.2)
Placebo | 5.5 (3.4) | 4.3 (2.8) | 22.8 (10.9) | 17.8 (7.5)

At Day 84, estradiol concentrations compared to Baseline concentrations were: 4.3 vs 3.9 pg/mL for 4 mcg; 4.8 vs 5.0 pg/mL for 10 mcg; and 4.4 vs 4.5 pg/mL for placebo.

Distribution

The distribution of exogenous estrogens is similar to that of endogenous estrogens. Estrogens are widely distributed in the body and are generally found in higher concentrations in the sex hormone target organs. Estrogens circulate in the blood largely bound to SHBG and albumin.

Metabolism

Exogenous estrogens are metabolized in the same manner as endogenous estrogens. Circulating estrogens exist in a dynamic equilibrium of metabolic interconversions. These transformations take place mainly in the liver. Estradiol is converted reversibly to estrone, and both can be converted to estriol, which is the major urinary metabolite. Estrogens also undergo enterohepatic recirculation via sulfate and glucuronide conjugation in the liver, biliary secretion of conjugates into the intestine, and hydrolysis in the intestine followed by reabsorption. In postmenopausal women, a significant portion of the circulating estrogens exist as sulfate conjugates, especially estrone sulfate, which serves as a circulating reservoir for the formation of more active estrogens.

Excretion

Estradiol, estrone, and estriol are excreted in the urine along with glucuronide and sulfate conjugates.

13 NONCLINICAL TOXICOLOGY

13.1 Carcinogenesis, Mutagenesis, Impairment of Fertility

Long-term continuous administration of natural and synthetic estrogens in certain animal species increases the frequency of carcinomas of the breast, uterus, cervix, vagina, testis, and liver.

14 CLINICAL STUDIES

14.1 Effects on Moderate to Severe Dyspareunia in Postmenopausal Women

The effectiveness and safety of IMVEXXY on moderate to severe dyspareunia, a symptom of vulvar and vaginal atrophy due to menopause were examined in one placebo-controlled clinical trial.

This 12-week, randomized, double-blind, placebo-controlled, parallel-group trial enrollee 574 generally healthy postmenopausal women between 40 to 75 years of age (mean 59 years of age) who at baseline assessment had ≤ 5% superficial cells on a vaginal smear, a vaginal pH > 5.0, and also identified, at baseline, moderate to severe dyspareunia as the most bothersome symptom to her. Greater than 90% of women also reported moderate to severe vaginal dryness at baseline. Treatment groups included 4 mcg IMVEXXY (N = 191), 10 mcg IMVEXXY (N = 191), and placebo (N = 192). All women were assessed for improvement in the mean change from Baseline to Week 12 for the co-primary efficacy variables of: most bothersome moderate to severe symptom of dyspareunia, percentage of vaginal superficial and percentage of vaginal parabasal cells on a vaginal smear, and vaginal pH.

IMVEXXY 4 mcg and 10 mcg inserts were statistically superior to placebo in reducing the severity of moderate to severe dyspareunia at Week 12 (see Table 3). A statistically significant increase in the percentage of superficial cells and a corresponding statistically significant decrease in the percentage of parabasal cells on a vaginal smear was also demonstrated for IMVEXXY 4 and 10 mcg inserts (p < 0.0001). The mean reduction in vaginal pH between Baseline and Week 12 was also statistically significant for IMVEXXY 4 and 10 mcg inserts (p < 0.0001).

Table 3: Efficacy of Dyspareunia Associated with Postmenopausal Vulvar and Vaginal Atrophy (Least Square Mean Change from Baseline to Week 12 in Severity of Woman's Self-Identified Most Bothersome Moderate to Severe Symptom of Vulvar and Vaginal Atrophy)
Most Bothersome Moderate to Severe Symptom at Baseline | IMVEXXY 4 mcg (N = 151) | IMVEXXY 10 mcg (N = 154) | Placebo (N = 163)
Dyspareunia
Baseline Mean (SD) | 2.7 (0.48) | 2.6 (0.48) | 2.7 (0.46)
LS Mean Change from Baseline (SE) | -1.52 (0.071) | -1.69 (0.071) | -1.28 (0.070)
p-value vs placebo | 0.0149 | <0.0001 | ------
The modified intent-to-treat population (MITT) included only women in the ITT population who at baseline met the inclusion criteria of ≤ 5% superficial cells on a vaginal smear, a vaginal pH > 5.0, and who identified moderate or severe dyspareunia as her most bothersome vaginal symptom.
Definitions: SD – standard deviation; SE – standard error; LS – least square

14.2 Women's Health Initiative Studies

The WHI enrolled approximately 27,000 predominantly healthy postmenopausal women in two substudies to assess the risks and benefits of daily oral CE (0.625 mg)-alone or in combination with MPA (2.5 mg) compared to placebo in the prevention of certain chronic diseases. The primary endpoint was the incidence of CHD (defined as nonfatal MI, silent MI and CHD death), with invasive breast cancer as the primary adverse outcome. A "global index" included the earliest occurrence of CHD, invasive breast cancer, stroke, PE, endometrial cancer (only in the CE plus MPA substudy), colorectal cancer, hip fracture, or death due to other causes. These substudies did not evaluate the effects of CE-alone or CE plus MPA on menopausal symptoms.

WHI Estrogen-Alone Substudy

The WHI estrogen-alone substudy was stopped early because an increased risk of stroke was observed, and it was deemed that no further information would be obtained regarding the risks and benefits of estrogen-alone in predetermined primary endpoints.

Results of the estrogen-alone substudy, which included 10,739 women (average 63 years of age, range 50 to 79; 75.3% White, 15.1% Black, 6.1% Hispanic, 3.6% Other) after an average follow-up of 7.1 years, are presented in Table 4.

Table 4: Relative and Absolute Risk Seen in the Estrogen-Alone Substudy of WHI [Adapted from numerous WHI publications. WHI publications can be viewed at www.nhlbi.nih.gov/whi.]
Event | Relative Risk CE vs Placebo (95% nCI [Nominal confidence intervals unadjusted for multiple looks and multiple comparisons.]) | CE N = 5,310 | Placebo N = 5,429
 |  | Absolute Risk per 10,000 Women-Years
CHD events [Results are based on centrally adjudicated data for an average follow-up of 7.1 years.] Non-fatal MI CHD death | 0.95 (0.78-1.16) 0.91 (0.73-1.14) 1.01 (0.71-1.43) | 54 40 16 | 57 43 16
A lStrokes Ischemic stroke | 1.33 (1.05-1.68) 1.55 (1.19-2.01) | 45 38 | 33 25
Deep vein thrombosis , [Not included in "global index."] | 1.47 (1.06-2.06) | 23 | 15
Pulmonary embolism | 1.37 (0.90-2.07) | 14 | 10
Invasive breast cancer | 0.80 (0.62-1.04) | 28 | 34
Colorectal cancer | 1.08 (0.75-1.55) | 17 | 16
Hip fracture | 0.65 (0.45-0.94) | 12 | 19
Vertebral fractures , | 0.64 (0.44-0.93) | 11 | 18
Lower arm/wrist fractures , | 0.58 (0.47-0.72) | 35 | 59
Total fractures , | 0.71 (0.64-0.80) | 144 | 197
Death due to other causes [Results are based on an average follow-up of 6.8 years.] , [All deaths, except from breast or colorectal cancer, definite or probable CHD, PE or cerebrovascular disease.] | 1.08 (0.88-1.32) | 53 | 50
Overall mortality , | 1.04 (0.88-1.22) | 79 | 75
Global Index [A subset of the events was combined in a "global index," defined as the earliest occurrence of CHD events, invasive breast cancer, stroke, pulmonary embolism, colorectal cancer, hip fracture, or death due to other causes.] | 1.02 (0.92-1.13) | 206 | 201

For those outcomes included in the WHI "global index" that reached statistical significance, the absolute excess risk per 10,000 women-years in the group treated with CE-alone was 12 more strokes while the absolute risk reduction per 10,000 women- years was 7 fewer hip fractures.^9The absolute excess risk of events included in the "global index" was a non-significant 5 events per 10,000 women-years. There was no difference between the groups in terms of all-cause mortality.

No overall difference for primary CHD events (nonfatal MI, silent MI and CHD death) and invasive breast cancer incidence in women receiving CE-alone compared with placebo was reported in final centrally adjudicated results from the estrogen-alone substudy, after an average follow-up of 7.1 years.

Centrally adjudicated results for stroke events from the estrogen-alone substudy, after an average follow-up of 7.1 years, reported no significant difference in distribution of stroke subtype or severity, including fatal strokes, in women receiving CE-alone compared to placebo. Estrogen-alone increased the risk for ischemic stroke, and this excess risk was present in all subgroups of women examined.^10

Timing of the initiation of estrogen-alone therapy relative to the start of menopause may affect the overall risk benefit profile. The WHI estrogen-alone substudy, stratified by age, showed in women 50-59 years of age a non-significant trend toward reduced risk for CHD [hazard ratio (HR) 0.63 (95% CI, 0.36 to 1.09)]and overall mortality [HR 0.71 (95% CI, 0.46 to 1.11)].

WHI Estrogen Plus Progestin Substudy

The WHI estrogen plus progestin substudy was stopped early. According to the predefined stopping rule, after an average follow-up of 5.6 years of treatment, the increased risk of invasive breast cancer and cardiovascular events exceeded the specified benefits included in the "global index." The absolute excess risk of events included in the "global index" was 19 per 10,000 women-years.

For those outcomes included in the WHI "global index" that reached statistical significance after 5.6 years of follow-up, the absolute excess risks per 10,000 women- years in the group treated with CE plus MPA were 7 more CHD events, 8 more strokes, 10 more PEs, and 8 more invasive breast cancers, while the absolute risk reductions per 10,000 women-years were 6 fewer colorectal cancers and 5 fewer hip fractures.

Results of the CE plus MPA substudy, which included 16,608 women (average 63 years of age, range 50 to 79; 83.9% White, 6.8% Black, 5.4% Hispanic, 3.9% Other) are presented in Table 5. These results reflect centrally adjudicated data after an average follow-up of 5.6 years.

Table 5: Relative and Absolute Risk Seen in the Estrogen Plus Progestin Substudy of WHI at an Average of 5.6 Years [Adapted from numerous WHI publications. WHI publications can be viewed at www.nhlbi.nih.gov/whi.] , [Results are based on centrally adjudicated data.]
Event | Relative Risk CE/MPA vs Placebo (95% nCI [Nominal confidence intervals unadjusted for multiple looks and multiple comparisons.]) | CE/MPA N = 8,506 | Placebo N = 8,102
 |  | Absolute Risk per 10,000 Women-Years
CHD events Non-fatal MI CHD death | 1.23 (0.99-1.53) 1.28 (1.00-1.63) 1.10 (0.70-1.75) | 41 31 8 | 34 25 8
A lStrokes Ischemic stroke | 1.31 (1.03-1.68) 1.44 (1.09-1.90) | 33 26 | 25 18
Deep vein thrombosis [Not included in "global index."] | 1.95 (1.43-2.67) | 26 | 13
Pulmonary embolism | 2.13 (1.45-3.11) | 18 | 8
Invasive breast cancer [Includes metastatic and non-metastatic breast cancer with the exception of in situ cancer.] | 1.24 (1.01-1.54) | 41 | 33
Colorectal cancer | 0.61 (0.42-0.87) | 10 | 16
Endometrial cancer | 0.81 (0.48-1.36) | 6 | 7
Cervical cancer | 1.44 (0.47-4.42) | 2 | 1
Hip fracture | 0.67 (0.47-0.96) | 11 | 16
Vertebral fractures | 0.65 (0.46-0.92) | 11 | 17
Lower arm/wrist fractures | 0.71 (0.59-0.85) | 44 | 62
Total fractures | 0.76 (0.69-0.83) | 152 | 199
Overa lmortality , [All deaths, except from breast or colorectal cancer, definite or probable CHD, PE or cerebrovascular disease.] | 1.00 (0.83-1.19) | 52 | 52
Global Index [A subset of the events was combined in a "global index," defined as the earliest occurrence of CHD events, invasive breast cancer, stroke, PE, colorectal cancer, hip fracture, or death due to other causes.] | 1.13 (1.02-1.25) | 184 | 165

Timing of the initiation of estrogen plus progestin therapy relative to the start of menopause may affect the overall risk benefit profile. The WHI estrogen plus progestin substudy stratified by age showed in women 50-59 years of age, a non-significant trend toward reduced risk for overall mortality [HR 0.69 (95% CI, 0.44 to 1.07)].

14.3 Women's Health Initiative Memory Study

The WHIMS estrogen-alone ancillary study of WHI enrolled 2,947 predominately healthy hysterectomized postmenopausal women 65 to 79 years of age and older (45% were 65 to 69 years of age; 36% were 70 to 74 years of age; 19% were 75 years of age and older) to evaluate the effects of daily CE (0.625 mg)-alone on the incidence of probable dementia (primary outcome) compared to placebo.

After an average follow-up of 5.2 years, the relative risk of probable dementia for CE- alone versus placebo was 1.49 (95% CI, 0.83 to 2.66). The absolute risk of probable dementia for CE-alone versus placebo was 37 versus 25 cases per 10,000 women- years. Probable dementia as defined in this study included Alzheimer's disease (AD), vascular dementia (VaD) and mixed types (having features of both AD and VaD). The most common classification of probable dementia in the treatment group and the placebo group was AD. Since the ancillary study was conducted in women 65 to 79 years of age, it is unknown whether these findings apply to younger postmenopausal women [see Warnings and Precautions (5.4), and Use in Specific Populations (8.5)] .

The WHIMS estrogen plus progestin ancillary study of WHI enrolled 4,532 predominantly healthy postmenopausal women 65 years of age and older (47% were 65 to 69 years of age; 35% were 70 to 74 years; 18% were 75 years of age and older) to evaluate the effects of daily CE (0.625 mg) plus MPA (2.5 mg) on the incidence of probable dementia (primary outcome) compared to placebo.

After an average follow-up of 4 years, the relative risk of probable dementia for CE plus MPA versus placebo was 2.05 (95% CI, 1.21 to 3.48). The absolute risk of probable dementia for CE plus MPA versus placebo was 45 versus 22 per 10,000 women-years. Probable dementia as defined in this study included AD, VaD and mixed types (having features of both AD and VaD). The most common classification of probable dementia in the treatment group and the placebo group was AD. Since the ancillary study was conducted in women 65 to 79 years of age, it is unknown whether these findings apply to younger postmenopausal women [see Warnings and Precautions (5.4), and Use in Specific Populations (8.5)].

When data from the two populations were pooled as planned in the WHIMS protocol, the reported overall relative risk for probable dementia was 1.76 (95% CI, 1.19 to 2.60). Differences between groups became apparent in the first year of treatment. It is unknown whether these findings apply to younger postmenopausal women [see Warnings and Precautions (5.4), and Use in Specific Populations (8.5)].

15 REFERENCES

1. Rossouw JE, et al. Postmenopausal Hormone Therapy and Risk of Cardiovascular Disease by Age and Years Since Menopause. JAMA. 2007; 297:1465-1477.
2. Hsia J, et al. Conjugated Equine Estrogens and Coronary Heart Disease. Arch Int Med. 2006; 166:357-365.
3. Curb JD, et al. Venous Thrombosis and Conjugated Equine Estrogen in Women Without a Uterus. Arch Int Med. 2006; 166:772-780.
4. Cushman M, et al. Estrogen Plus Progestin and Risk of Venous Thrombosis. JAMA. 2004; 292:1573-1580.
5. Stefanick ML, et al. Effects of Conjugated Equine Estrogens on Breast Cancer and Mammography Screening in Postmenopausal Women with Hysterectomy. JAMA. 2006; 295:1647-1657.
6. Chlebowski RT, et al. Influence of Estrogen Plus Progestin on Breast Cancer and Mammography in Healthy Postmenopausal Women. JAMA. 2003; 289:3243-3253.
7. Anderson GL, et al. Effects of Estrogen Plus Progestin on Gynecologic Cancers and Associated Diagnostic Procedures. JAMA. 2003; 290:1739-1748.
8. Shumaker SA, et al. Conjugated Equine Estrogens and Incidence of Probable Dementia and Mild Cognitive Impairment in Postmenopausal Women. JAMA. 2004; 291:2947-2958.
9. Jackson RD, et al. Effects of Conjugated Equine Estrogen on Risk of Fractures and BMD in Postmenopausal Women with Hysterectomy: Results from the Women's Health Initiative Randomized Trial. J Bone Miner Res. 2006; 21:817-828.
10. Hendrix SL, et al. Effects of Conjugated Equine Estrogen on Stroke in the Women's Health Initiative. Circulation. 2006; 113:2425-2434.

16 HOW SUPPLIED/STORAGE AND HANDLING

16.1 How Supplied

IMVEXXY (estradiol vaginal inserts) are small, light pink, tear-shaped inserts for manual placement into the vagina. Inserts contain 4 mcg or 10 mcg of estradiol. Each insert is imprinted in white ink on one side with "04" or "10" corresponding to the insert's dosage strengths.

IMVEXXY (estradiol vaginal inserts), 4 mcg and 10 mcg, are provided in opaque push- through blisters and are packaged in cartons containing either 18 inserts for the starter pack or 8 inserts for the maintenance pack.

IMVEXXY 4 mcg | 8 inserts | NDC 50261-104-08
IMVEXXY 4 mcg | 18 inserts | NDC 50261-104-18
IMVEXXY 10 mcg | 8 inserts | NDC 50261-110-08
IMVEXXY 10 mcg | 18 inserts | NDC 50261-110-18

Keep out of reach of children. Packages are not child-resistant.

16.2 Storage and Handling

Store at 20°C to 25ºC (68°F to 77ºF), excursions permitted to 15ºC to 30ºC (59ºF to 86ºF). [See USP Controlled Room Temperature.]

17 PATIENT COUNSELING INFORMATION

Advise women to read the FDA-approved patient labeling (Patient Information and Instructions for Use).

Vaginal Bleeding

Inform postmenopausal women of the importance of reporting vaginal bleeding to their healthcare provider as soon as possible [see Warnings and Precautions (5.3)].

Possible Serious Adverse Reactions with Estrogen-Alone Therapy

Inform postmenopausal women of possible serious adverse reactions of estrogen-alone therapy including Cardiovascular Disorders, Malignant Neoplasms, and Probable Dementia [see Warnings and Precautions (5.2, 5.3, 5.4)].

Possible Common Adverse Reactions with Estrogen-Alone Therapy

Inform postmenopausal women of possible less serious but common adverse reactions of estrogen-alone therapy such as headache, breast pain and tenderness, nausea and vomiting.

PATIENT INFORMATION
IMVEXXY (ĭm vex' ee)
(estradiol vaginal inserts)

Read this Patient Information before you start using IMVEXXY and each time you get a refill. There may be new information. This information does not take the place of talking to your healthcare provider about your menopausal symptoms or your treatment.

What is the most important information I should know about IMVEXXY (an estrogen hormone)?

- Using estrogen-alone may increase your chance of getting cancer of the uterus (womb).
- Report any unusual vaginal bleeding right away while you are using IMVEXXY. Vaginal bleeding after menopause may be a warning sign of cancer of the uterus (womb). Your healthcare provider should check any unusual vaginal bleeding to find out the cause.
- Do not use estrogen-alone to prevent heart disease, heart attacks, strokes, or dementia (decline of brain function).
- Using estrogen-alone may increase your chances of getting strokes or blood clots.
- Using estrogen-alone may increase your chance of getting dementia, based on a study of women 65 years of age and older.
- Do not use estrogens with progestogens to prevent heart disease, heart attacks, strokes or dementia.
- Using estrogens with progestogens may increase your chances of getting heart attacks, strokes, breast cancer, or blood clots.
- Using estrogens with progestogens may increase your chance of getting dementia, based on a study of women 65 years of age and older.
- Only one estrogen-alone product and dose have been shown to increase your chances of getting strokes, blood clots, and dementia. Only one estrogen with progestogen product and dose have been shown to increase your chances of getting heart attacks, strokes, breast cancer, blood clots, and dementia. Because other products and doses have not been studied in the same way, it is not known how the use of IMVEXXY will affect your chances of having these conditions.
- You and your healthcare provider should talk regularly about whether you still need treatment with IMVEXXY.

What is IMVEXXY?
IMVEXXY is a prescription medicine that contains an estrogen hormone in a vaginal insert.

What is IMVEXXY used for?
IMVEXXY is used after menopause to treat moderate to severe painful intercourse, a symptom of changes in and around your vagina, due to menopause.

Who should not use IMVEXXY?
Do not start using IMVEXXY if you:

- have unusual vaginal bleeding.
  Vaginal bleeding after menopause may be a warning sign of cancer of the uterus (womb). Your healthcare provider should check any unusual vaginal bleeding to find out the cause.
- have been diagnosed with a bleeding disorder.
- currently have or have had certain cancers.
  Estrogens may increase the chances of getting certain types of cancers, including cancer of the breast or uterus (womb). If you have or have had cancer, talk with your healthcare provider about whether you should use IMVEXXY.
- currently have or have had blood clots.
- had a stroke or heart attack.
- currently have or have had liver problems.
- are allergic to IMVEXXY or any of its ingredients.See the list of ingredients in IMVEXXY at the end of this leaflet.

Before you use IMVEXXY, tell your healthcare provider about all of your medical conditions, including if you:

- have any unusual vaginal bleeding.Vaginal bleeding after menopause may be a warning sign of cancer of the uterus (womb). Your healthcare provider should check any unusual vaginal bleeding or spotting to find out the cause.
- have any other medical conditions that may become worse while you are using IMVEXXY.Your healthcare provider may need to check you more carefully if you have certain medical conditions, such as asthma (wheezing), epilepsy (seizures), diabetes, migraine, endometriosis, lupus, angioedema (swelling of face and tongue), problems with your heart, liver, thyroid, kidneys, or have high calcium levels in your blood.
- are going to have surgery or will be on bed rest.You may need to stop using IMVEXXY.
- are pregnant or think you may be pregnant.Imvexxy is not for pregnant women.
- are breast feeding.The hormone in IMVEXXY can pass into your breast milk.

Tell your healthcare provider about all the medicines you take,including prescription and over-the-counter medicines, vitamins, and herbal supplements.
Some medicines may affect how IMVEXXY works.

IMVEXXY may also affect how other medicines work. Keep a list of your medicines and show it to your healthcare provider and pharmacist when you get new medicine.

How should I use IMVEXXY?
For detailed instructions, see the step-by-step instructions for using IMVEXXY at the end of this Patient Information.

- Use IMVEXXY exactly as your healthcare provider tells you to use it.
- IMVEXXY is a vaginal insert that you place in your vagina.
- IMVEXXY is only for use in the vagina. Do nottake IMVEXXY by mouth (orally).
- Estrogens should be used at the lowest dose possible for your treatment and for only as long as needed.
- Put 1 IMVEXXY insert inside your vagina, 1 time a day at about the same time for the first two weeks.
- Then put 1 IMVEXXY insert into your vagina two times a week, every three to four days (for example, Monday and Thursday), for as long as you use IMVEXXY.
- You and your healthcare provider should talk regularly (for example, every 3 to 6 months) about the dose you are using and whether you still need treatment with IMVEXXY.

What are the possible side effects of IMVEXXY?
Side effects are grouped by how serious they are and how often they happen when you are treated.
Serious, but less common side effects could include:

- heart attack
- breast cancer
- dementia
- gallbladder disease
- high levels of fat (triglyceride) in your blood
- enlargement of benign tumors of the uterus ("fibroids")
- stroke
- cancer of the lining of the uterus (womb)

- high or low blood calcium
- visual abnormalities
- liver problems
- worsening of swelling of face and tongue (angioedema) in women with a history of angioedema
- blood clots
- cancer of the ovary
- high blood pressure
- changes in your thyroid hormone levels

Call your healthcare provider right away if you get any of the following warning signs or any other unusual symptoms that concern you:

- new breast lumps
- unusual vaginal bleeding
- changes in vision or speech
- sudden, new, severe headaches
- severe pains in your chest or legs with or without shortness of breath, weakness, and fatigue

Common side effects of IMVEXXY include:

- headache
- breast tenderness or pain
- nausea and vomiting

These are not all of the possible side effects of IMVEXXY. For more information, ask your healthcare provider or pharmacist. Tell your healthcare provider if you have any side effects that bother you or that do not go away.
Call your doctor for medical advice about side effects. You may report side effects to FDA at 1-800-FDA-1088. You may also report side effects to Mayne Pharma at 1- 844-825-8500.

What can I do to lower my chances of a serious side effect with IMVEXXY?

- Talk with your healthcare provider regularly about whether you should continue using IMVEXXY.
- If you have a uterus (womb), talk with your healthcare provider about whether the addition of a progestogen is right for you. In general, the addition of a progestogen is recommended for a woman with a uterus to reduce the chance of getting cancer of the uterus.
- See your healthcare provider right away if you get vaginal bleeding while using®IMVEXXY.
- Have a pelvic exam, breast exam, and mammogram (breast X-ray) every year unless your healthcare provider tells you something else. If members of your family have had breast cancer or if you have had breast lumps or an abnormal mammogram, you may need to have breast exams more often.
- If you have high blood pressure, high cholesterol (fat in the blood), diabetes, are overweight, or if you use tobacco, you may have a higher chance of getting heart disease. Ask your healthcare provider for ways to lower your chances of getting heart disease.

General information about the safe and effective use of IMVEXXY.
Medicines are sometimes prescribed for purposes other than those listed in a Patient Information leaflet. Do not use IMVEXXY for a condition for which it was not prescribed. Do not give IMVEXXY to other people, even if they have the same symptoms you have. It may harm them. You can ask your pharmacist or healthcare provider for information about IMVEXXY that is written for health professionals

What are the ingredients in IMVEXXY?
Active ingredient:IMVEXXY (estradiol vaginal inserts) are small, light pink, tear-shaped inserts that contain estradiol.
Inactive ingredients: Each insert also contains ammonium hydroxide, ethanol, ethyl acetate, ethylene glycol palmitostearate, FD&C Red #40, gelatin, glycerin, isopropyl alcohol, lecithin, medium chain triglycerides, polyethylene glycol, polyethylene glycol stearates, polyvinyl acetate phthalate, propylene glycol, purified water, sorbitol-sorbitan solution, and titanium dioxide. IMVEXXY is supplied in blister cartons of 18 or 8 vaginal inserts.

Instructions For Use IMVEXXY® (ĭm vex' ee) (estradiol vaginal inserts)

Read this Instructions for Use before you start using IMVEXXY and each time you get a refill. There may be new information. This information does not take the place of talking to your healthcare provider about your menopausal symptoms or your treatment.

How should I use IMVEXXY?

- IMVEXXY is an insert only for use in the vagina. Do not take by mouth.
- Put 1 IMVEXXY insert inside your vagina, 1 time a day at about the same time for the first two weeks, then put 1 IMVEXXY insert into your vagina two times a week, every three to four days (for example, Monday and Thursday), for as long as you use IMVEXXY.
- Write down the days you will put in your IMVEXXY insert.
- Wash and dry your hands before handling the IMVEXXY insert.

Step 1:Push 1 IMVEXXY insert through the foil of the blister package.

Figure A

Step 2:Hold the IMVEXXY insert with the larger end between your fingers.

Figure B

Step 3:Select the best position for vaginal insertion that is most comfortable for you to put in the IMVEXXY insert. See Figure Cfor suggested insertion in the lying down position or Figure D for suggested insertion in the standing position. With the smaller end up, put the insert about two inches into your vagina using your finger.

Figure C

or

Figure D

If you have any questions, please ask your healthcare provider or pharmacist.

How should I store IMVEXXY?

- Store IMVEXXY at room temperature between 68°F to 77°F (20°C to 25°C). IMVEXXY
- packaging is not child-resistant.

Keep IMVEXXY and al medicines out of the reach of children.

For information, go to TherapeuticsMD.comor call TherapeuticsMD, Inc. at 1-877-833- 0176

Manufactured for: TherapeuticsMD, Inc., Boca Raton, FL 33431

For patent information, go to TherapeuticsMD.com/patentsIMVEXXY is a registered trademark of TherapeuticsMD, Inc.
© TherapeuticsMD, Inc. All rights reserved.

The Patient Information and Instructions for Use have been approved by the U.S. Food and Drug Administration.

Revised: 11/2023

PACKAGE LABEL

Principal Display Panel - Imvexxy 4 mcg 8 Count Carton Label

NDC 50261-104-08

Rx only

Imvexxy®

4 mcg(estradiol vaginal inserts)

TherapeuticsMD®

8 vaginal inserts

FOR VAGINAL USE ONLY

PACKAGE LABEL

Principal Display Panel - Imvexxy 4 mcg 18 Count Carton Label

NDC 50261-104-18

Rx only

Imvexxy®

4 mcg(estradiol vaginal inserts)

TherapeuticsMD®

18 vaginal inserts

FOR VAGINAL USE ONLY

PACKAGE LABEL

Principal Display Panel - Imvexxy 10 mcg 8 Count Carton Label

NDC 50261-110-08

Rx only

Imvexxy®

10 mcg(estradiol vaginal inserts)

TherapeuticsMD®

8 vaginal inserts

FOR VAGINAL USE ONLY

PACKAGE LABEL

Principal Display Panel - Imvexxy 10 mcg 18 Count Carton Label

NDC 50261-110-18

Rx only

Imvexxy®

10 mcg(estradiol vaginal inserts)

TherapeuticsMD®

18 vaginal inserts

FOR VAGINAL USE ONLY